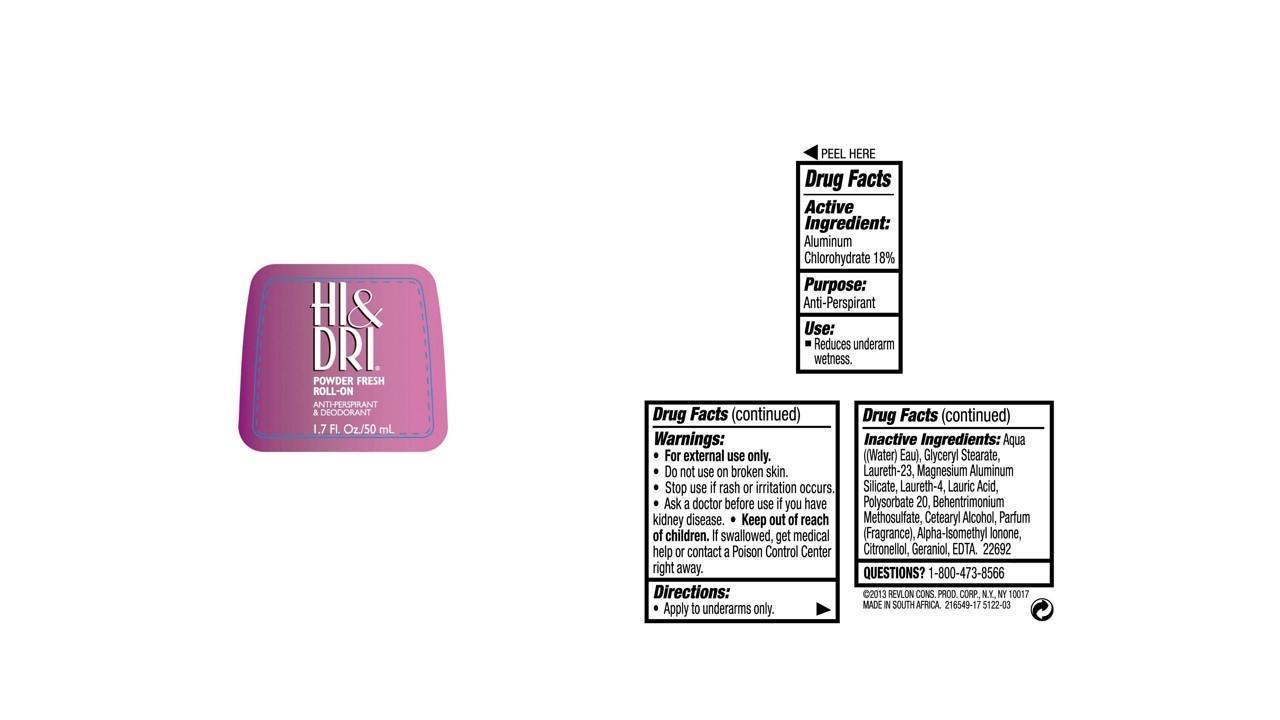 DRUG LABEL: HI AND DRI ANTIPERSPIRANT
NDC: 10967-057 | Form: LIQUID
Manufacturer: Revlon Consumer Products Corp
Category: otc | Type: HUMAN OTC DRUG LABEL
Date: 20131209

ACTIVE INGREDIENTS: ALUMINUM CHLOROHYDRATE 0.18 g/1 mL
INACTIVE INGREDIENTS: WATER; GLYCERYL MONOSTEARATE; LAURETH-23; MAGNESIUM ALUMINUM SILICATE; LAURETH-4; LAURIC ACID; CETOSTEARYL ALCOHOL; BEHENTRIMONIUM METHOSULFATE; EDETIC ACID; ISOMETHYL-.ALPHA.-IONONE; .BETA.-CITRONELLOL, (R)-; GERANIOL; LIMONENE, (+)-; HYDROXYCITRONELLAL; BENZYL ALCOHOL; BENZYL SALICYLATE; LINALOOL, (+)-; CITRAL

Hi & Dri Roll-On Antiperspirant - Powder Fresh 1.7 fl. oz (50 ml)

Drug Facts Active Ingredient

Aluminum chlorohydrate 18%

Purpose

Antiperspirant

Use

- Reduces underarm wetness

Warnings:

For external use only.

Do not use on broken skin

Ask a doctor before use if you have kidney disease

Stop use if rash or irriation occurs

Keep out of reach of children.

If swallowed, get medical help or contact a Poison Control Center right away.

Directions

Apply to underarms only.

Inactive Ingredients

aqua((water) eau), glyceryl stearate, laureth-23, magnesium aluminum silicate, laureth-4, lauric acid, cetearyl alcohol, behentrimonium methosulfate, edta, alpha-isomethyl ionone, citronellol, limonene, hydroxycitronellol, benzyl alcohol, benzyl salicylate, linalool, citral

Questions

1-800-473-8566